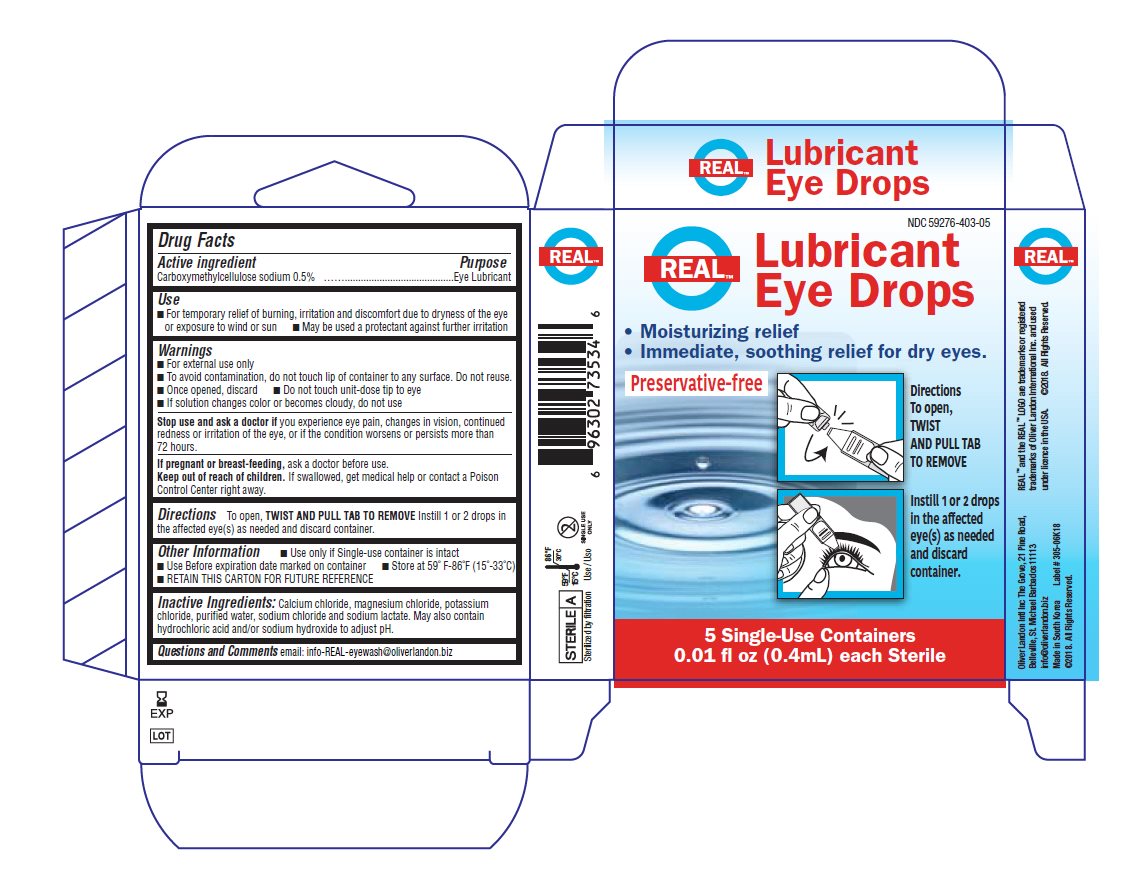 DRUG LABEL: Real
NDC: 59276-403 | Form: SOLUTION/ DROPS
Manufacturer: Oliver Landon Intl Inc.
Category: otc | Type: HUMAN OTC DRUG LABEL
Date: 20211205

ACTIVE INGREDIENTS: CARBOXYMETHYLCELLULOSE SODIUM 5 mg/1 mL
INACTIVE INGREDIENTS: CALCIUM CHLORIDE; MAGNESIUM CHLORIDE; POTASSIUM CHLORIDE; WATER; SODIUM CHLORIDE; SODIUM LACTATE; HYDROCHLORIC ACID; SODIUM HYDROXIDE

Real Lubricant Eye Drops

Drug Facts

Active ingredient

Carboxymethylcellulose sodium 0.5%

Purpose

Eye Lubricant

Use

- For temporary relief of burning, irritation and discomfort due to dryness of the eye or exposure to wind or sun
- May be used as a protectant against further irritation

Warnings

- For external use only
- To avoid contamination, do not touch tip of container to any surface. Do not reuse.
- Once opened, discard
- Do not touch unit-dose tip to eye
- If solution changes color or becomes cloudy, do not use

Stop use and ask a doctor if you experience eye pain, changes in vision, continued redness or irritation of the eye, or if the condition worsens or persists for more than 72 hours.

PREGNANCY OR BREAST FEEDING

If pregnant or breast-feeding, ask a doctor before use.

Keep out of reach of children. If swallowed, get medical help or contact a Poison Control Center right away.

Directions

To open, TWIST AND PULL TAB TO REMOVE. Instill 1 or 2 drops in the affected eye(s) as needed and discard container.

*If used for post-operative dryness and discomfort, follow your eye doctor’s instructions.

Other information

- Use only if single-use container is intact
- Use before expiration date marked on container
- Store at 59°-86°F (15°-33°C)
- RETAIN THIS CARTON FOR FUTURE REFERENCE

INACTIVE INGREDIENT

Inactive ingredients Calcium chloride, magnesium chloride, potassium chloride, purified water, sodium chloride and sodium lactate. May also contain hydrochloric acid and/or sodium hydroxide to adjust pH.

Questions or Comments?

info@oliverlandon.biz

PACKAGE LABEL

NDC 59276-403-05

Real
Lubricant Eye Drops

- Moisturizing relief
- Immediate, soothing relief for dry eyes.

Preservative-free

Directions
To open, TWIST AND PULL TAB TO REMOVE

Instill 1 or 2 drops in the affected eye(s) as needed and discard container.
5 Single-Use Containers
0.01 fl oz (0.4 mL) each Sterile